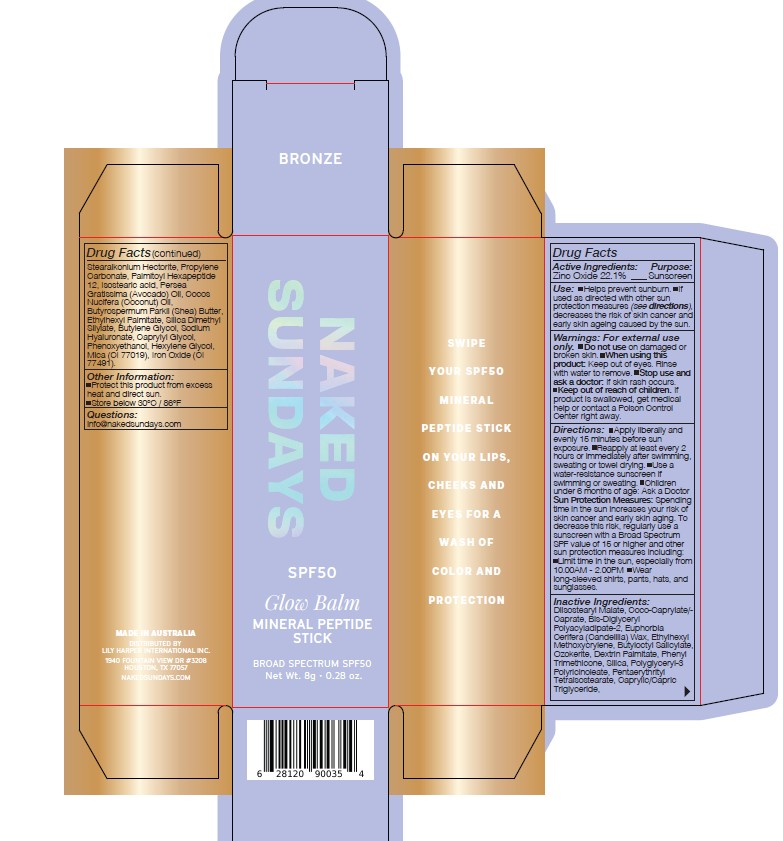 DRUG LABEL: Naked Sundays Glow Balm Mineral Peptide Stick Broad Spectrum SPF50 Bronze 8g
NDC: 81104-104 | Form: STICK
Manufacturer: NAKED SUNDAYS PTY LTD
Category: otc | Type: HUMAN OTC DRUG LABEL
Date: 20250322

ACTIVE INGREDIENTS: ZINC OXIDE 22.1 g/100 g
INACTIVE INGREDIENTS: BUTYLOCTYL SALICYLATE; PALMITOYL HEXAPEPTIDE-12; ISOSTEARIC ACID; SILICA DIMETHYL SILYLATE; CAPRYLYL GLYCOL; DIISOSTEARYL MALATE; BIS-DIGLYCERYL POLYACYLADIPATE-2; SODIUM HYALURONATE; HEXYLENE GLYCOL; ETHYLHEXYL PALMITATE; BROWN IRON OXIDE; COCO-CAPRYLATE/CAPRATE; STEARALKONIUM HECTORITE; PHENYL TRIMETHICONE; POLYGLYCERYL-3 PENTARICINOLEATE; BUTYLENE GLYCOL; CAPRYLIC/CAPRIC TRIGLYCERIDE; ETHYLHEXYL METHOXYCRYLENE; PHENOXYETHANOL; PROPYLENE CARBONATE; PERSEA GRATISSIMA (AVOCADO) OIL; BUTYROSPERMUM PARKII (SHEA) BUTTER; MICA; SILICA; EUPHORBIA CERIFERA (CANDELILLA) WAX; CERESIN; DEXTRIN PALMITATE (CORN; 20000 MW); PENTAERYTHRITYL TETRAISOSTEARATE; COCOS NUCIFERA (COCONUT) OIL

Naked Sundays Glow Balm Mineral Peptide Stick Broad Spectrum SPF50 Bronze 8g

Active Ingredients

Zinc Oxide 22.1 %

uses

SPF Product

DOSAGE AND ADMINISTRATION

Directions: Shake well before use.
Apply liberally and reapply every 80 minutes,
especially after swimming or towel drying.
Sun Protection Measures Spending time in
the sun increases your risk of skin cancer and
early skin aging. To decrease this risk, regularly
use a sunscreen with a Broad Spectrum SPF
value of 15 or higher and other sun protection
measures including: Limit time in the sun,
especially from 10 am-2 pm Wear longsleeved
shirts, pants, hats, and sunglasses For
Children under 6 months of age ask a doctor.

Warning

Warnings: For external use only. Do not use
on damaged or broken skin Avoid prolonged
sun exposure. If it gets in your eyes, wash well
with water. Keep out of reach of children.
Stop use and ask a doctor if rashes occur.
If product is swallowed, get medical help or
contact a Poison Control Center right away.

INACTIVE INGREDIENTS

INACTIVE INGREDIENTS: Bis-Diglyceryl Polyacyladipate-2, Butylene Glycol, Butyloctyl Salicylate, Butyrospermum Parkii (Shea) Butter, Caprylic/Capric Triglyceride, Caprylyl Glycol, Coco-Caprylate/Caprate, Cocos Nucifera (Coconut) Oil, Dextrin Palmitate, Diisostearyl Malate, Ethylhexyl Methoxycrylene, Ethylhexyl Palmitate, Euphorbia Cerifera (Candelilla) Wax, Hexylene Glycol, Iron Oxides, Isostearic acid, Mica, Ozokerite, Palmitoyl Hexapeptide‐12, Pentaerythrityl Tetraisostearate, Persea Gratissima (Avocado) Oil, Phenoxyethanol, Phenyl Trimethicone, Polyglyceryl-3 Polyricinoleate, Propylene Carbonate, Silica, Silica Dimethyl Silylate, Sodium Hyaluronate, Stearalkonium Hectorite

Other Information:

Other Information: Protect this product
from excess heat and direct sun. Store below
30°C / 86°F.

Questions: info@nakedsundays.com

INDICATIONS AND USAGE

Uses: Helps prevent sunburn. If used as
directed with other sun protection measures
(see directions), decreases the risk of skin
cancer and early skin ageing caused by the sun.

KEEP OUT OF REACH OF CHILDREN

Warnings: For external use only. Do not use
on damaged or broken skin Avoid prolonged
sun exposure. If it gets in your eyes, wash well
with water. Keep out of reach of children.
Stop use and ask a doctor if rashes occur.
If product is swallowed, get medical help or
contact a Poison Control Center right away.